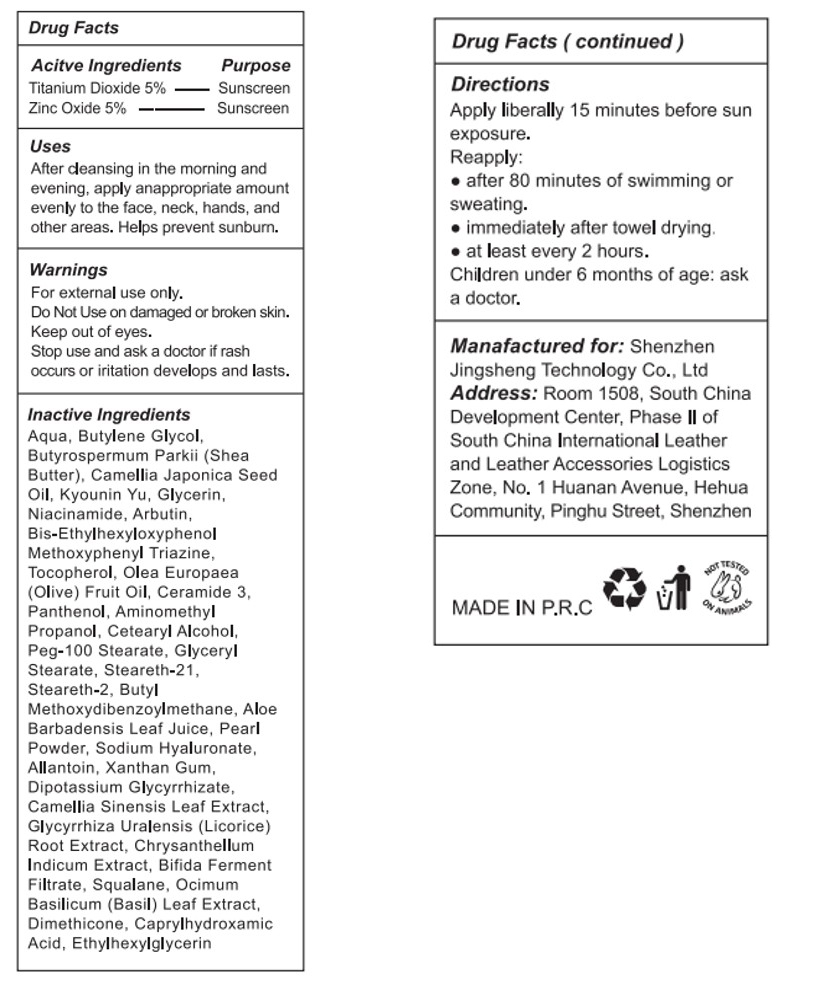 DRUG LABEL: WMK Bleaching Cream with Sunscreen SPF 30
NDC: 85354-001 | Form: CREAM
Manufacturer: Shenzhen Jingsheng Technology Co., Ltd
Category: otc | Type: HUMAN OTC DRUG LABEL
Date: 20250313

ACTIVE INGREDIENTS: TITANIUM DIOXIDE 5 g/100 mL; ZINC OXIDE 5 g/100 mL
INACTIVE INGREDIENTS: BUTYLENE GLYCOL; STEARETH-21; CHRYSANTHELLUM INDICUM TOP; SQUALANE; TOCOPHEROL; PEG-100 STEARATE; BUTYL METHOXYDIBENZOYLMETHANE; AMINOMETHYL PROPANOL; DIPOTASSIUM GLYCYRRHIZATE; OCIMUM BASILICUM (BASIL) LEAF; ALLANTOIN; CAMELLIA JAPONICA SEED OIL; BUTYROSPERMUM PARKII (SHEA) BUTTER; CETOSTEARYL ALCOHOL; STEARETH-2; APRICOT KERNEL OIL; AQUA; PEARL (HYRIOPSIS CUMINGII); SODIUM HYALURONATE; CAMELLIA SINENSIS LEAF; BIFIDOBACTERIUM BIFIDUM; DIMETHICONE; ETHYLHEXYLGLYCERIN; ARBUTIN; CERAMIDE 3; XANTHAN GUM; GLYCERIN; NIACINAMIDE; CAPRYLHYDROXAMIC ACID; OLEA EUROPAEA (OLIVE) FRUIT OIL; BIS-ETHYLHEXYLOXYPHENOL METHOXYPHENYL TRIAZINE; ALOE BARBADENSIS LEAF POWDER; GLYCYRRHIZA URALENSIS ROOT; PANTHENOL; GLYCERYL STEARATE

WMK Bleaching Cream with Sunscreen SPF 30+

ACTIVE INGREDIENT

Titanium Dioxide 5%
Zinc Oxide 5%

PURPOSE

Sunscreen

INDICATIONS AND USAGE

After deansing in the morning andevening, apply anappropriate amountevenly to the face, neck, hands, andother areas. Helps prevent sunbum.

WARNINGS

For external use only.
Do Not Use on damaged or broken skin.
Keep out of eyes.
Stop use and ask a doctor if rashoccurs or iritation develops and lasts.

Do Not Use on damaged or broken skin.

WHEN USING

Keep out of eyes.

Stop use and ask a doctor if rashoccurs or iritation develops and lasts.

KEEP OUT OF REACH OF CHILDREN SECTION

DOSAGE AND ADMINISTRATION

Apply liberally 15 minutes before sun exposure.
Reapply:
after 80 minutes of swimming orsweating.
immediately after towel drying
at least every 2 hours.Children under 6 months of age: ask
a doctor.

INACTIVE INGREDIENT

AQUA
BUTYLENE GLYCOL
BUTYROSPERMUM PARKII (SHEA BUTTER)
CAMELLIA JAPONICA SEED OIL
KYOUNIN YU
GLYCERIN
NIACINAMIDE
ARBUTIN
BIS-ETHYLHEXYLOXYPHENOL METHOXYPHENYL TRIAZINE
TOCOPHEROL
OLEA EUROPAEA (OLIVE) FRUIT OIL
CERAMIDE 3
PANTHENOL
AMINOMETHYL PROPANOL
CETEARYL ALCOHOL
PEG-100 STEARATE
GLYCERYL STEARATE
STEARETH-21
STEARETH-2
BUTYL METHOXYDIBENZOYLMETHANE
ALOE BARBADENSIS LEAF JUICE
PEARL POWDER
SODIUM HYALURONATE
ALLANTOIN
XANTHAN GUM
DIPOTASSIUM GLYCYRRHIZATE
CAMELLIA SINENSIS LEAF EXTRACT
GLYCYRRHIZA URALENSIS (LICORICE) ROOT EXTRACT
CHRYSANTHELLUM INDICUM EXTRACT
BIFIDA FERMENT FILTRATE
SQUALANE
OCIMUM BASILICUM (BASIL) LEAF EXTRACT
DIMETHICONE
CAPRYLHYDROXAMIC ACID
ETHYLHEXYLGLYCERIN